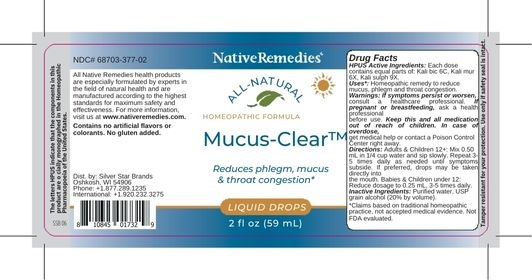 DRUG LABEL: Mucus-Clear
NDC: 68703-377 | Form: LIQUID
Manufacturer: Silver Star Brands
Category: homeopathic | Type: HUMAN OTC DRUG LABEL
Date: 20250101

ACTIVE INGREDIENTS: POTASSIUM DICHROMATE 6 [hp_C]/59 mL; POTASSIUM CHLORIDE 6 [hp_X]/59 mL; POTASSIUM SULFATE 9 [hp_X]/59 mL
INACTIVE INGREDIENTS: WATER; ALCOHOL

NativeRemedies® Mucus-Clear™

HPUS Active Ingredients: kali bic 6C, Kali mur 6X, Kali sulph 9X.

Uses*:

Uses*: Homeopathic remedy to reduce mucus, phlegm and throat congestion.

*Claims based on traditional homeopathic practice, not accepted medical evidence. Not FDA evaluated.

Directions

Directions: Adults & Children 12+: Mix 0.50 mL in 1/4 cup water and sip slowly. Repeat 3-5 times daily as needed until symptoms subside. If preferred, drops may be taken directly into the mouth. Babies & Children under 12: Reduce dosage to 0.25mL, 3-5times daily.

Warnings

Warnings: If symptoms persist or worsen, consult a healthcare professional. If pregnant or breastfeeding, ask a health professional before use. Keep this and all medication out of reach of children. In case of overdose, get medical help or contact Poison Control Center right away.

OTHER SAFETY INFORMATION

Contains no artificial flavors or colorants. No gluten added.

Tamper resistant for your protection. use only if safety seal is intact.

Inactive Ingredients

Inactive Ingredients: Purified water, USP grain alcohol(20% by volume).

KEEP OUT OF REACH OF CHILDREN

Keep this and all medication out of reach of children.

PREGNANCY OR BREAST FEEDING

If pregnant or breastfeeding, ask a health professional before use.

PURPOSE

Reduces phlegm, mucus & throat congestion*

*This statement has not been evaluated by the Food and Drug Administration. This product is not intended to diagnose, treat, cure or prevent any disease.